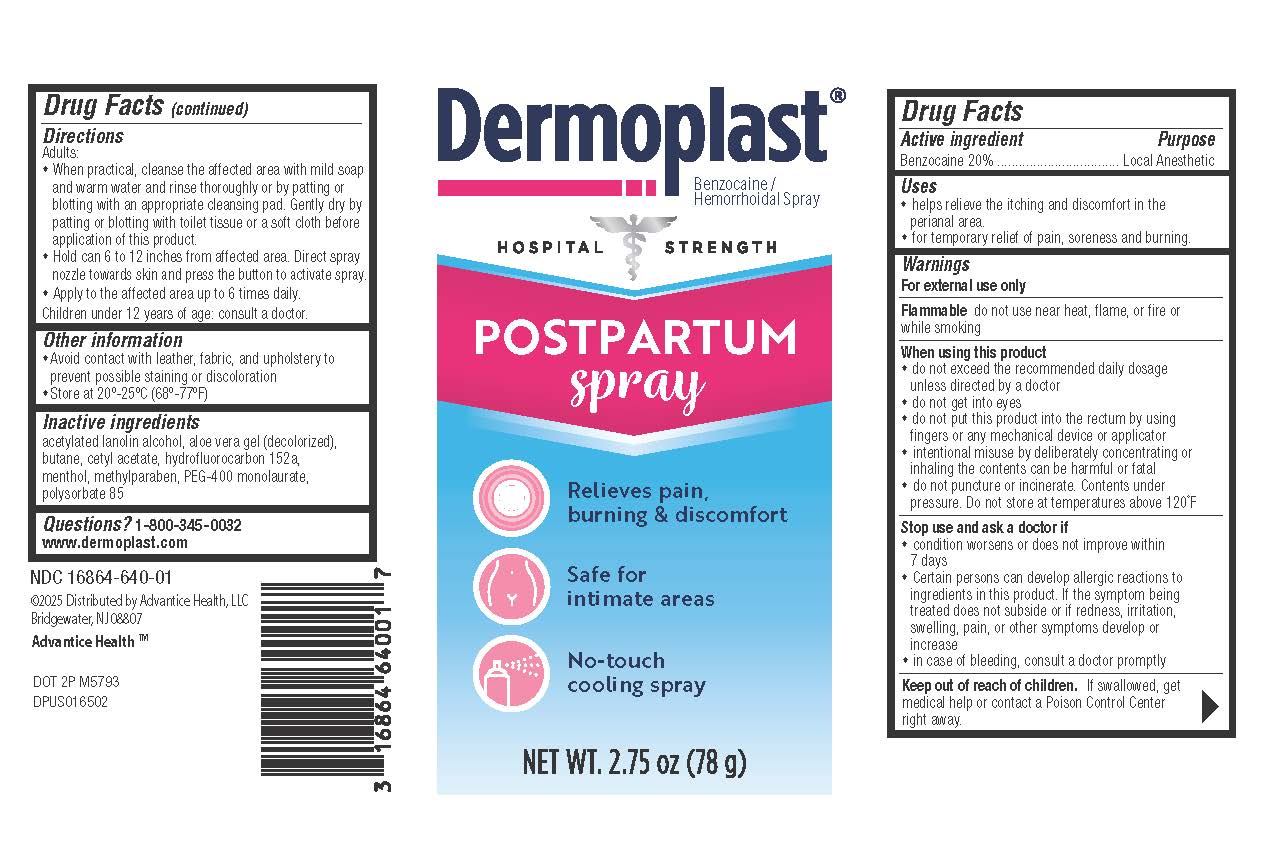 DRUG LABEL: Dermoplast Post Partum
NDC: 16864-640 | Form: AEROSOL, SPRAY
Manufacturer: Advantice Health, LLC
Category: otc | Type: HUMAN OTC DRUG LABEL
Date: 20250611

ACTIVE INGREDIENTS: BENZOCAINE 200 mg/1 g
INACTIVE INGREDIENTS: POLYSORBATE 85; CETYL ACETATE; 1,1-DIFLUOROETHANE; METHYLPARABEN; BUTANE; MENTHOL; PEG-8 LAURATE; ALOE VERA LEAF; ACETYLATED LANOLIN ALCOHOLS

Dermoplast Post Partum Spray

Ingredient: Benzocaine 20% Purpose: Local Anesthetic

DOSAGE AND ADMINISTRATION

• When practical, cleanse the affected area with mild soap and warm water and rinse thoroughly or by patting and blotting with an appropriate cleansing pad.
• Gently dry by patting or blotting with toilet tissue or a soft cloth before application of this product.
• Hold can 6 to 12 inches away from affected area. Direct the spray nozzle towards the skin and press the button to activate spray.
• Apply to the affected area up to 6 times daily.
• Children under 12 years of age: consult a doctor.

INACTIVE INGREDIENT

acetylated lanolin alcohol, aloe vera gel (decolorized), butane, cetyl acetate, hydrofluorocarbon 152a, methylparaben USP, PEG-400 monolaurate, menthol, polysorbate 85

WARNINGS

For external use only
Flammable: do not use near heat, flame, or fire or while smoking
When using this product:
• Do not exceed the recommended daily dosage unless directed by a doctor.
• Do not get into eyes.
• Do not put this product into the rectum by using fingers or any mechanical device or applicator.
• Intentional misuse by deliberately concentrating or inhaling the contents can be harmful or fatal.
• Do not puncture or incinerate. Contents under pressure.
• Do not store at temperatures above 120°F.
Stop use and ask a doctor if:
• Condition worsens or does not improve within 7 days.
• Certain persons can develop allergic reactions to ingredients in this product. If the symptom being treated does not subside or if redness, irritation, swelling, pain, or other symptoms develop or increase.
• In case of bleeding, consult a doctor promptly
Keep out of reach of children. If swallowed, get medical help or contact a Poison Control Center right away.

INDICATIONS AND USAGE

• helps relieve the itching and discomfort in the perianal area. • for temporary relief of pain, soreness and burning.

Keep out of reach of children. If swallowed, get medical help or contact a Poison Control Center right away.

PURPOSE

Local Anesthetic